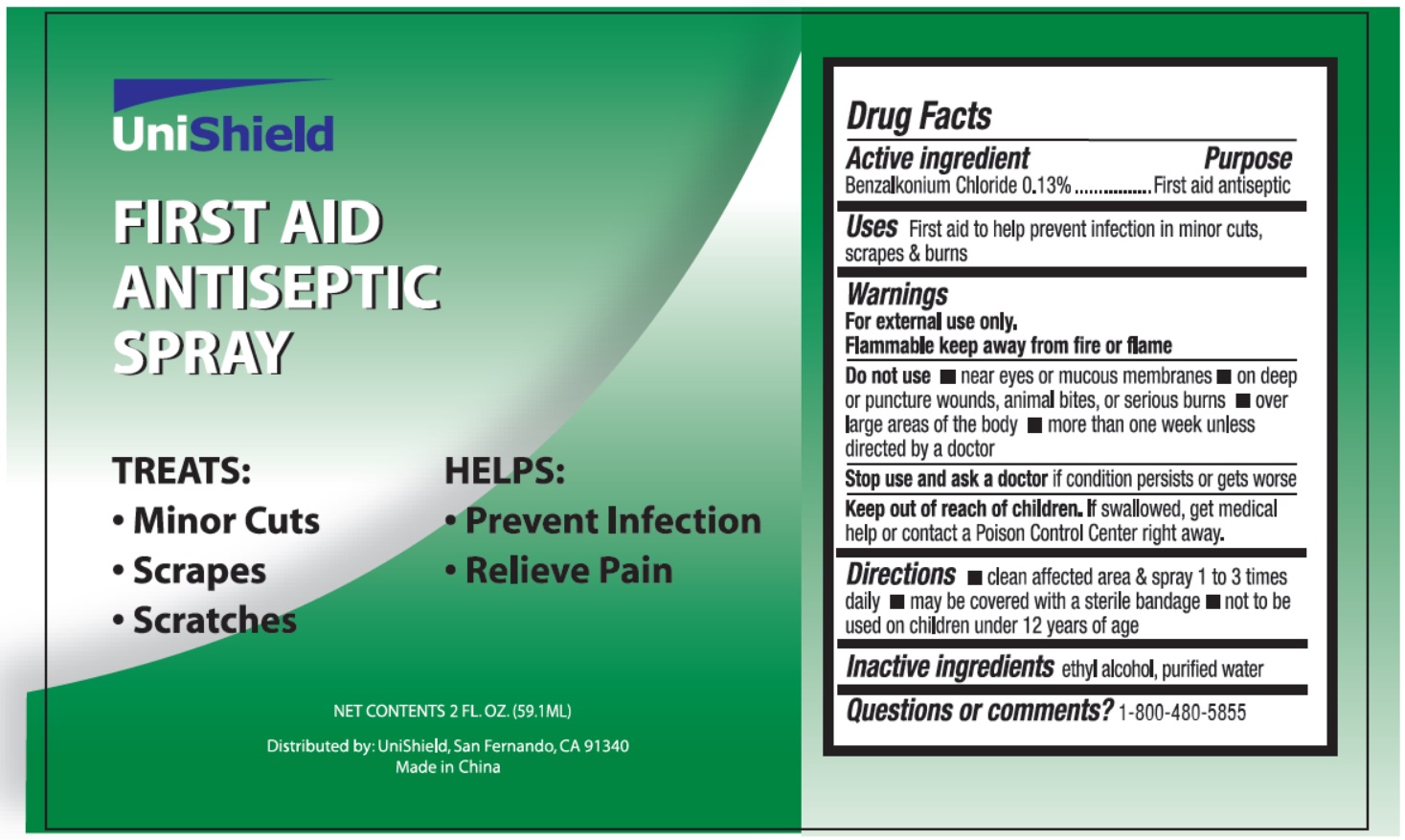 DRUG LABEL: First Aid Antispetic
NDC: 49314-0001 | Form: SPRAY
Manufacturer: Unishield
Category: otc | Type: HUMAN OTC DRUG LABEL
Date: 20250928

ACTIVE INGREDIENTS: BENZALKONIUM CHLORIDE 0.13 mg/1 mL
INACTIVE INGREDIENTS: WATER; ALCOHOL

49314-0001-1 Unishield
First Aid Antiseptic spray

Active ingredient

Benzalkonium chloride 0.13%

Purpose

First aid antiseptic

Uses

first aid to help prevent infection in minor cuts, scrapes and burns

Warnings

For external use only

Flammable keep away from fire or flame

Do not use

- near eyes or mucous membranes
- on deep or puncture wounds , animal bites, or serious burns
- over large areas of the body
- more than one week unless directed by a doctor

Stop use and ask a doctor

if condition persists or gets worse

Keep out of reach of children.

If swallowed, get medical help or contact a Poison Control Center right away.

Directions

- clean affected area & spray 1 to 3 times daily
- may be covered with a sterile bandage
- not to be used on children under 12 of years of age

Inactive ingredients

ethyl alcohol, purified water

Questions or comments？

1-800-480-5855